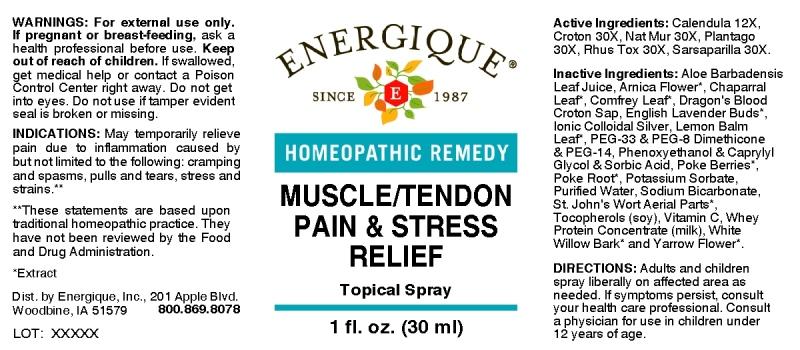 DRUG LABEL: Muscle/Tendon Pain and Stress Relief
NDC: 44911-0303 | Form: SPRAY
Manufacturer: Energique, Inc.
Category: homeopathic | Type: HUMAN OTC DRUG LABEL
Date: 20241029

ACTIVE INGREDIENTS: CALENDULA OFFICINALIS FLOWERING TOP 12 [hp_X]/1 mL; CROTON TIGLIUM SEED 30 [hp_X]/1 mL; SODIUM CHLORIDE 30 [hp_X]/1 mL; PLANTAGO MAJOR WHOLE 30 [hp_X]/1 mL; TOXICODENDRON PUBESCENS LEAF 30 [hp_X]/1 mL; SMILAX ORNATA ROOT 30 [hp_X]/1 mL
INACTIVE INGREDIENTS: ALOE VERA LEAF; ARNICA MONTANA FLOWER; LARREA TRIDENTATA TOP; COMFREY LEAF; CROTON LECHLERI RESIN; LAVANDULA ANGUSTIFOLIA FLOWER; SILVER; MELISSA OFFICINALIS LEAF; POLYETHYLENE GLYCOL 1500; PEG-8 DIMETHICONE; POLYETHYLENE GLYCOL 700; PHENOXYETHANOL; CAPRYLYL GLYCOL; SORBIC ACID; PHYTOLACCA AMERICANA FRUIT; PHYTOLACCA AMERICANA ROOT; POTASSIUM SORBATE; WATER; SODIUM BICARBONATE; HYPERICUM PERFORATUM; .ALPHA.-TOCOPHEROL; ASCORBIC ACID; WHEY; SALIX ALBA BARK; ACHILLEA MILLEFOLIUM FLOWER

DRUG FACTS:

ACTIVE INGREDIENTS:

Calendula Officinalis 12X, Croton Tiglium 30X, Natrum Muriaticum 30X, Plantago Major 30X, Rhus Tox 30X, Sarsaparilla (Smilax Regelii) 30X.

INDICATIONS:

May temporarily relieve pain due to inflammation caused by but not limited to the following: cramping and spasms, pulls and tears, stress and strains.**

**These statements are based upon traditional homeopathic practice. They have not been reviewed by the Food and Drug Administration.

WARNINGS:

For external use only.

If pregnant or breast-feeding, ask a health professional before use.

Keep out of reach of children. If swallowed, get medical help or contact a Poison Control Center right away.

Do not get into eyes.

If symptoms persist, consult a doctor.

Do not use if tamper evident seal is broken or missing.

Keep out of reach of children. If swallowed, get medical help or contact a Poison Control Center right away.

DIRECTIONS:

Adults and children spray liberally on affected area as needed. If symptoms persist, consult your health care professional. Consult a physician for use in children under 12 years of age.

INDICATIONS:

May temporarily relieve pain due to inflammation caused by but not limited to the following: cramping and spasms, pulls and tears, stress and strains.**

**These statements are based upon traditional homeopathic practice. They have not been reviewed by the Food and Drug Administration.

INACTIVE INGREDIENTS:

Aloe Barbadensis Leaf Juice (Aloe Vera 10X Concentrate), Arnica Montana (Flower)*, Larrea Tridentata (Leaf)*, Symphytum Officinale (Leaf)*, Croton Lechleri (Sap), Lavandula Angustifolia (Buds)*, Ionic Colloidal Silver Base, Melissa Officinalis (Leaf)*, [Peg-33, Peg-8 Dimethicone, Peg-14 (Silsense Copolyol-1 Silicone)], [Phenoxyethanol, Caprylyl Glycol, Sorbic Acid, (Optiphen-Plus)], Phytolacca Americana (Berries)*, Phytolacca Americana (Root)*, Potassium Sorbate, Purified Water, Sodium Bicarbonate, Hypericum Perforatum (Aerial Parts)*, Tocopherol [Vitamin E Oil] (Derived From Soy Bean), Vitamin C Powder (Ascorbic Acid), Whey Protein Concentrate, Salix Alba (Bark)*, Achillea Millefolium (Flower)*
*Extract

QUESTIONS:

Dist. by Energique, Inc., 201 Apple Blvd.
Woodbine, IA 51579 800.869.8078

PACKAGE LABEL DISPLAY:

ENERGIQUE

SINCE 1987

HOMEOPATHIC REMEDY

MUSCLE/TENDON

PAIN & STRESS

RELIEF

Topical Spray

1 fl. oz. (30 ml)